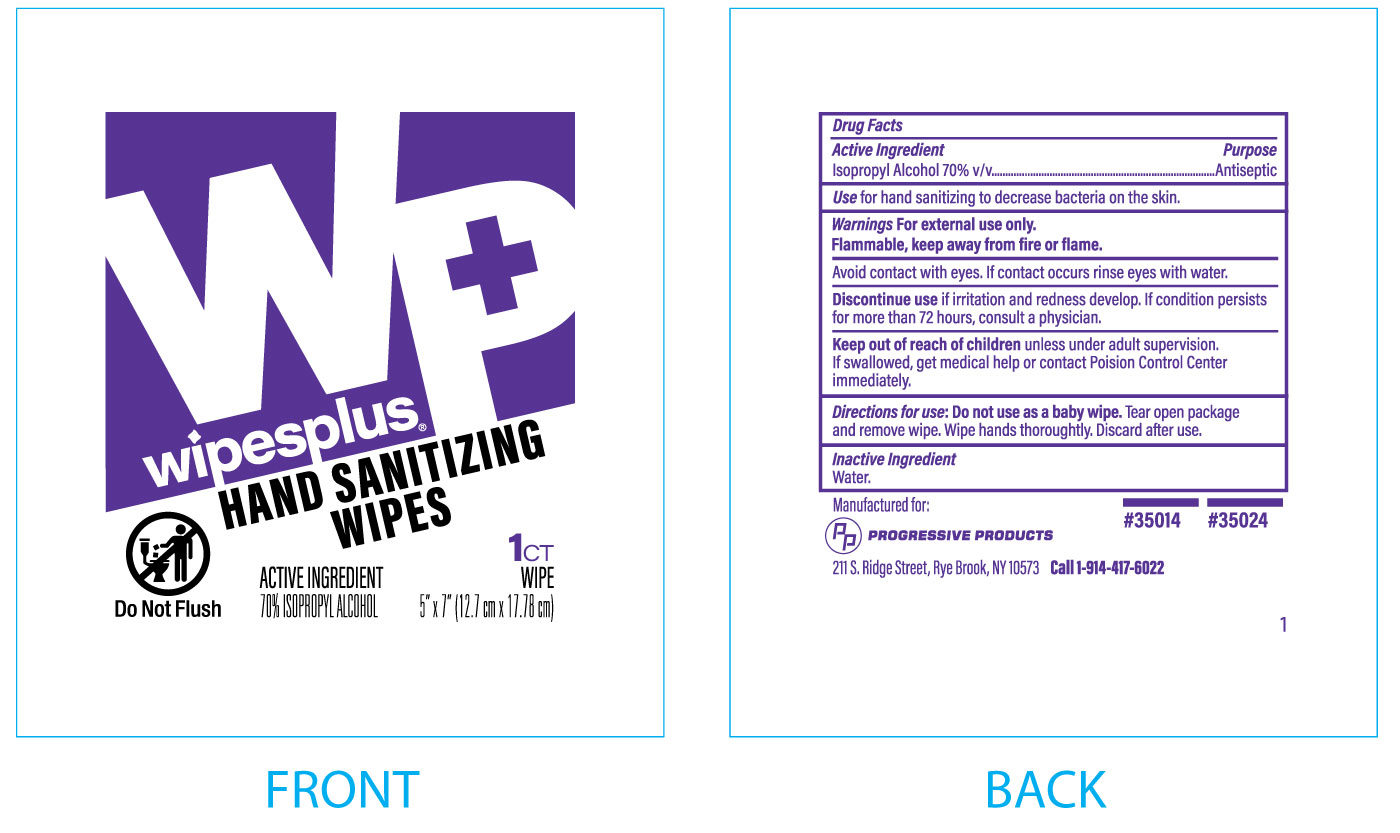 DRUG LABEL: Wipesplus Hand Sanitizing Wipes
NDC: 0924-0251 | Form: SWAB
Manufacturer: Acme United Corporation
Category: otc | Type: HUMAN OTC DRUG LABEL
Date: 20241126

ACTIVE INGREDIENTS: ISOPROPYL ALCOHOL 70 mL/100 mL
INACTIVE INGREDIENTS: WATER

Wipesplus Hand Sanitizing Wipes

Active Ingredient

Isopropyl Alcohol 70% v/v

Purpose

Antiseptic

Use

for hand sanitizing to decrease bacteria on the skin.

Warnings

For external use only.

Flammable, keep away from fire or flame.

Avoid contact with eyes. If contact occurs, rinse eyes with water.

Discontinue use if irritation and redness develop. If condition persists for more than 72 hours, consult a physician

Keep our of reach of children

Keep out of the reach of children unless under adult supervision. If swallowed, get medical help or contact Poison Control Center immediately.

Directions for use:

Do not use as a baby wipe. Tear open package and remove wipe. Wipe hands thoroughly. Discard after use.

Inactive Ingredient

Water.

PACKAGE LABEL

packet image